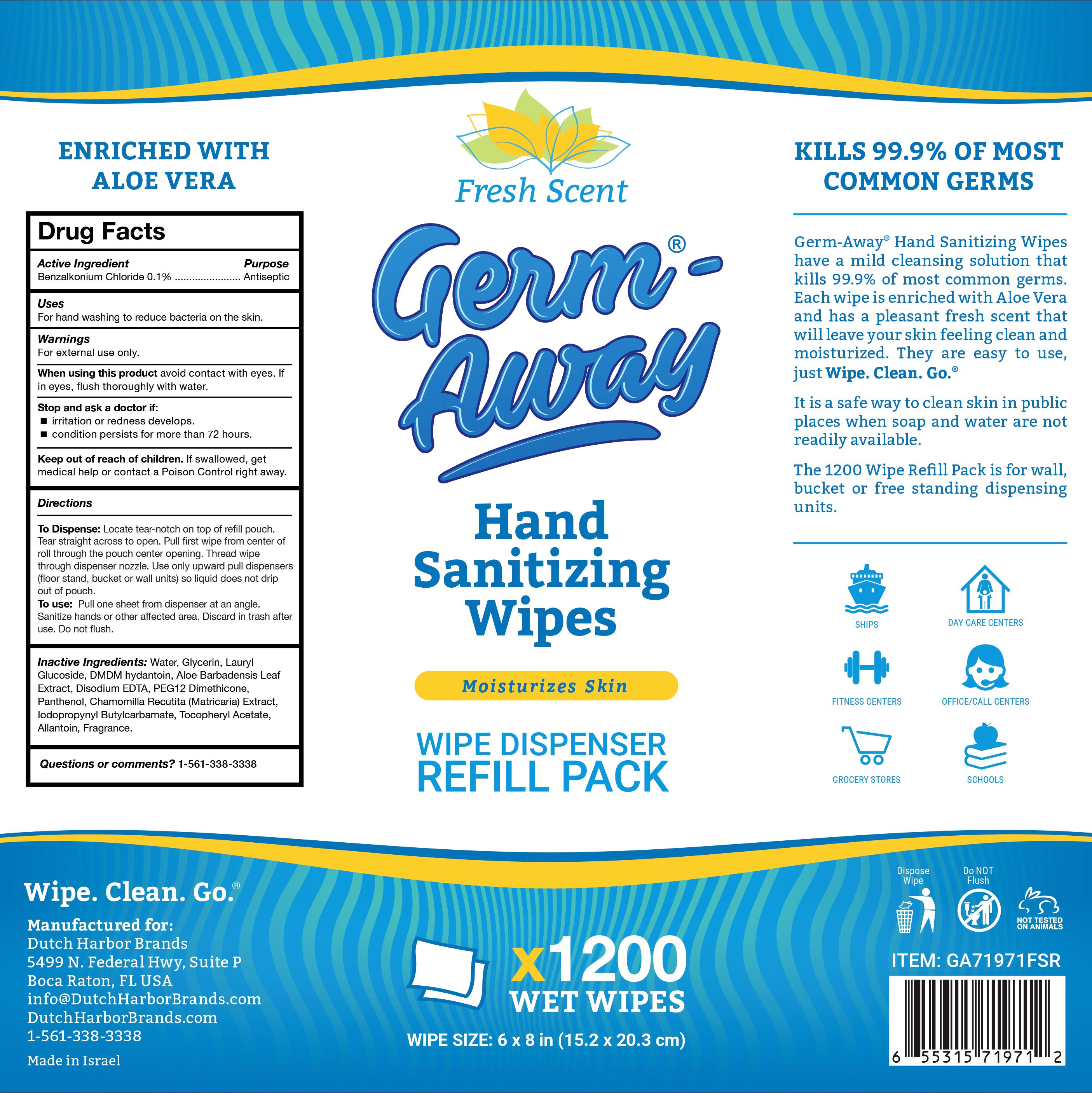 DRUG LABEL: Germ-Away
NDC: 74680-112 | Form: CLOTH
Manufacturer: Unico International Trading Corp
Category: otc | Type: HUMAN OTC DRUG LABEL
Date: 20260108

ACTIVE INGREDIENTS: BENZALKONIUM CHLORIDE 1 mg/1 g
INACTIVE INGREDIENTS: DECYL GLUCOSIDE; ALLANTOIN; PEG-12 DIMETHICONE (300 CST); .ALPHA.-TOCOPHEROL ACETATE; EDETATE SODIUM; SODIUM BENZOATE; VIRIDIFLOROL; TETRAHYDROLINALOOL; ANHYDROUS CITRIC ACID; PANTHENOL; SODIUM HYDROXYMETHYLGLYCINATE; ALOE VERA LEAF; WATER; CHAMOMILE; 2,2'-OXYDIPROPANOL; 4-TERT-BUTYLCYCLOHEXYL ACETATE; GLYCERIN; POTASSIUM SORBATE

Germ-Away

Active ingredient

Active ingredient 0.1%

Purpose

Anti-bacterial

Keep out of the reach of children except under adult supervision.

Inactive ingredients

potassium sorbate, sodium hydroxymethylglycinate, aloe vera leaf, anhydrous citric acid, panthenol, water, decyl glucoside, chamomile, allantoin, peg-12 dimethicone, alpha-tocopherol acetate, edetate sodium, glycerin, sodium benzoate, fragrance

Directions

Pull one sheet from dispenser at an angle. Sanitize hands or other affected area. Discard in trash after use. Do not flush.

To dispense

Locate tear-notch on top of refill pouch. Tear straight across to open. Pull first wipe from center of roll through the pouch center opening. Thread wipe through dispenser nozzle. Use only upward pull dispensers (floor stand, bucket or wall units) so liquid does not drip out of pouch.

Warnings

Warning section - for external use only. Do not use in the eyes. Keep out of eyes. In case of eye contact rinse with water. If irritation develops, just continue use. Consult doctor if your condition persists for more than 72 hours. If swallowed, seek medical attention or contact a Poison Control Center.